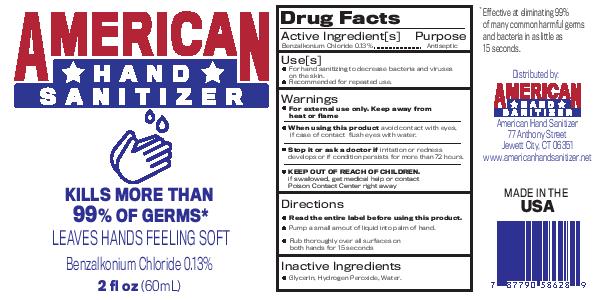 DRUG LABEL: American Hand Sanitizer
NDC: 79421-001 | Form: SPRAY
Manufacturer: American Hand Sanitizer, LLC
Category: otc | Type: HUMAN OTC DRUG LABEL
Date: 20200813

ACTIVE INGREDIENTS: BENZALKONIUM CHLORIDE 1.3 g/1 mL
INACTIVE INGREDIENTS: HYDROGEN PEROXIDE; WATER; GLYCERIN

ACTIVE INGREDIENT

Benzalkonium Chloride 0.13%

PURPOSE

Anitseptic

INDICATIONS AND USAGE

For hand sanitizing to decrease bacteria and viruses on the skin.

Recommended for repeated use.

Warnings

For external use only.

When using this product avoid contact with eyes.

In case of eye contact, flush eyes with water.

STOP USE

Stop it and ask a doctor if irritation or redness develops, or if condition persists for more than 72 hours.

Keep out of the reach of children.

If swallowed, get medical help or contact a Poison Control Center right away.

DOSAGE AND ADMINISTRATION

Read the entire label before using this product.

Pump a small amount of liquid into palm of hand.

Rub thoroughly over all surfaces of both hands for 15 seconds.

INACTIVE INGREDIENT

Glycerin, Hydrogen Peroxide, Water

Questions?

1-866-443-4509